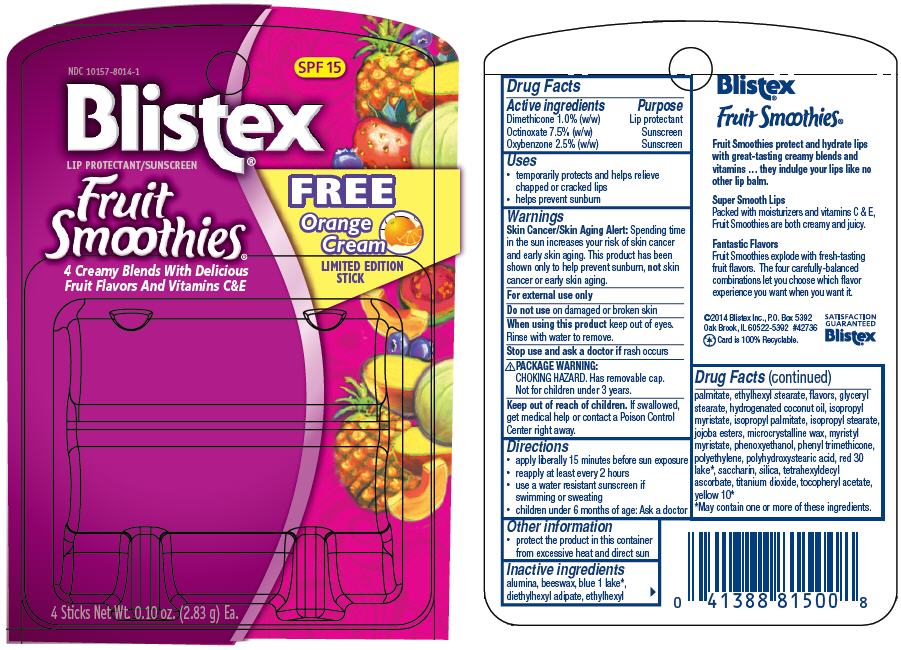 DRUG LABEL: Fruit Smoothies
NDC: 10157-8014 | Form: KIT | Route: TOPICAL
Manufacturer: Blistex Inc.
Category: otc | Type: HUMAN OTC DRUG LABEL
Date: 20140616

ACTIVE INGREDIENTS: Dimethicone 1 g/100 g; Octinoxate 7.5 g/100 g; Oxybenzone 2.5 g/100 g; Dimethicone 1 g/100 g; Octinoxate 7.5 g/100 g; Oxybenzone 2.5 g/100 g; Dimethicone 1 g/100 g; Octinoxate 7.5 g/100 g; Oxybenzone 2.5 g/100 g; Dimethicone 1 g/100 g; Octinoxate 7.5 g/100 g; Oxybenzone 2.5 g/100 g
INACTIVE INGREDIENTS: aluminum oxide; yellow wax; diethylhexyl adipate; glyceryl monostearate; ethylhexyl palmitate; isopropyl myristate; microcrystalline wax; myristyl myristate; phenoxyethanol; ethylhexyl stearate; silicon dioxide; hydrogenated coconut oil; isopropyl palmitate; isopropyl stearate; tetrahexyldecyl ascorbate; titanium dioxide; phenyl trimethicone; high density polyethylene; saccharin; .alpha.-tocopherol acetate; aluminum oxide; yellow wax; diethylhexyl adipate; glyceryl monostearate; ethylhexyl palmitate; isopropyl myristate; microcrystalline wax; myristyl myristate; phenoxyethanol; ethylhexyl stearate; silicon dioxide; hydrogenated coconut oil; isopropyl palmitate; isopropyl stearate; tetrahexyldecyl ascorbate; titanium dioxide; phenyl trimethicone; high density polyethylene; D&C red no. 30; D&C yellow no. 10; saccharin; .alpha.-tocopherol acetate; aluminum oxide; yellow wax; diethylhexyl adipate; glyceryl monostearate; ethylhexyl palmitate; isopropyl myristate; microcrystalline wax; myristyl myristate; phenoxyethanol; ethylhexyl stearate; silicon dioxide; hydrogenated coconut oil; isopropyl palmitate; isopropyl stearate; tetrahexyldecyl ascorbate; titanium dioxide; phenyl trimethicone; high density polyethylene; FD&C blue no. 1; D&C yellow no. 10; saccharin; .alpha.-tocopherol acetate; aluminum oxide; yellow wax; diethylhexyl adipate; glyceryl monostearate; ethylhexyl palmitate; isopropyl myristate; microcrystalline wax; myristyl myristate; phenoxyethanol; ethylhexyl stearate; silicon dioxide; hydrogenated coconut oil; isopropyl palmitate; isopropyl stearate; tetrahexyldecyl ascorbate; titanium dioxide; phenyl trimethicone; high density polyethylene; FD&C blue no. 1; D&C red no. 30; saccharin; .alpha.-tocopherol acetate

Fruit Smoothies®

Drug Facts

ACTIVE INGREDIENT

Active ingredients | Purpose
Dimethicone 1.0% (w/w) | Lip protectant
Octinoxate 7.5% (w/w) | Sunscreen
Oxybenzone 2.5% (w/w) | Sunscreen

Uses

- temporarily protects and helps relieve chapped or cracked lips
- helps prevent sunburn

Warnings

Skin Cancer/Skin Aging Alert

Spending time in the sun increases your risk of skin cancer and early skin aging. This product has been shown only to help prevent sunburn, not skin cancer or early skin aging.

For external use only

Do not use on damaged or broken skin

When using this product keep out of eyes. Rinse with water to remove.

Stop use and ask a doctor if rash occurs

PACKAGE WARNING

CHOKING HAZARD. Has removable cap. Not for children under 3 years.

Keep out of reach of children. If swallowed, get medical help or contact a Poison Control Center right away.

Directions

- apply liberally 15 minutes before sun exposure
- reapply at least every 2 hours
- use a water resistant sunscreen if swimming or sweating
- children under 6 months of age: Ask a doctor

Other information

- protect the product in this container from excessive heat and direct sun

Inactive ingredients

alumina, beeswax, blue 1 lake [May contain one or more of these ingredients.] , diethylhexyl adipate, ethylhexyl palmitate, ethylhexyl stearate, flavors, glyceryl stearate, hydrogenated coconut oil, isopropyl myristate, isopropyl palmitate, isopropyl stearate, jojoba esters, microcrystalline wax, myristyl myristate, phenoxyethanol, phenyl trimethicone, polyethylene, polyhydroxystearic acid, red 30 lake, saccharin, silica, tetrahexyldecyl ascorbate, titanium dioxide, tocopheryl acetate, yellow 10

PRINCIPAL DISPLAY PANEL - Kit Blister Pack

NDC 10157-8014-1

SPF 15

Blistex®

LIP PROTECTANT/SUNSCREEN

Fruit
Smoothies®

4 Creamy Blends With Delicious
Fruit Flavors And Vitamins C&E

FREE
Orange
Cream
LIMITED EDITION
STICK

4 Sticks Net Wt. 0.10 oz. (2.83 g) Ea.